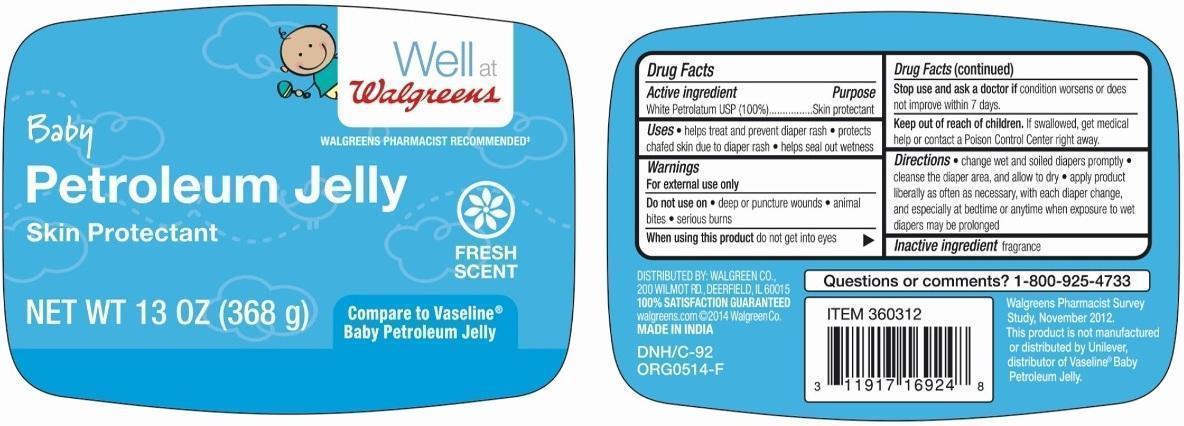 DRUG LABEL: Walgreens Baby Petroleum
NDC: 0363-0731 | Form: JELLY
Manufacturer: Walgreen Company
Category: otc | Type: HUMAN OTC DRUG LABEL
Date: 20260114

ACTIVE INGREDIENTS: PETROLATUM 100 g/100 g

Walgreens® BABY PETROLEUM JELLY

Active ingredient

White Petrolatum USP (100%)

Purpose

Skin protectant

Uses

- helps treat and prevent diaper rash
- protects chafed skin due to diaper rash
- helps seal out wetness

Warnings

For external use only.

Do not use on

- deep or puncture wounds
- animal bites
- serious burns

When using this productdo not get into eyes.

Stop use and ask a doctor ifcondition worsens or does not improve within 7 days.

Keep out of reach of children

If swallowed, get medical help or contact a Poison Control Center right away.

Directions

- change wet and soiled diapers promptly
- cleanse the diaper area, and allow to dry
- apply product liberally as often as necessary, with each diaper change, and especially at bedtime or anytime when exposure to wet diapers may be prolonged

Inactive ingredient

Fragrance

Questions or comments?

1-800-925-4733

Package/Label Principal Display Panel

Baby Petroleum Jelly

Skin Protectant

Fresh Scent

Compare to Vaseline®Baby Petroleum Jelly

NET WT 13 OZ (368 g)